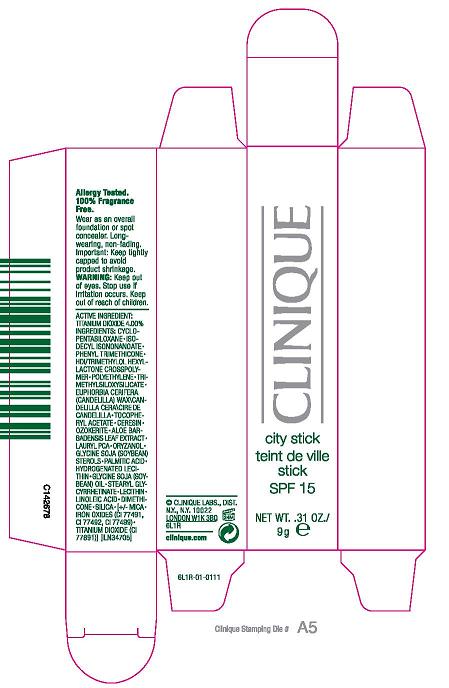 DRUG LABEL: CITY STICK
NDC: 49527-001 | Form: STICK
Manufacturer: CLINIQUE LABORATORIES INC
Category: otc | Type: HUMAN OTC DRUG LABEL
Date: 20100330

ACTIVE INGREDIENTS: TITANIUM DIOXIDE 4.0 g/100 g

ACTIVE INGREDIENT: TITANIUM DIOXIDE, 4%

USAGE: KEEP TIGHTLY CAPPED TO AVOID PRODUCT SHRINKAGE

WARNINGS

WARNING: KEEP OUT OF EYES. STOP USE IF IRRITATION OCCURS. KEEP OUT OF REACH OF CHILDREN

PACKAGE LABEL

CLINIQUE CITY STICK SPF 15

0.31 OZ/ 9 g

CLINIQUE LABS, DISTR.
NY, NY 10022
CLINQUE.COM